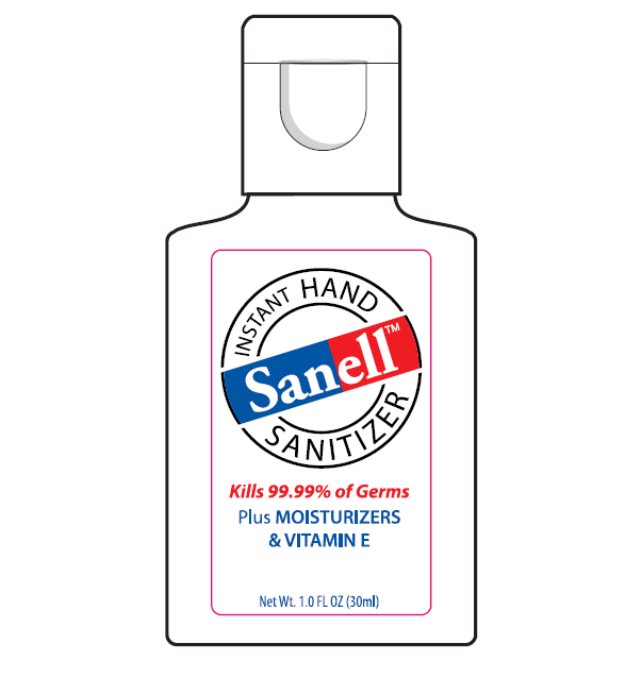 DRUG LABEL: Sanell Hand Sanitizer
NDC: 63645-166 | Form: GEL
Manufacturer: OraLabs
Category: otc | Type: HUMAN OTC DRUG LABEL
Date: 20221111

ACTIVE INGREDIENTS: ALCOHOL 58.10 mg/1 g
INACTIVE INGREDIENTS: .ALPHA.-TOCOPHEROL ACETATE 0.010 mg/1 g; CARBOMER HOMOPOLYMER TYPE C (ALLYL PENTAERYTHRITOL CROSSLINKED) .310 mg/1 g; PROPYLENE GLYCOL .500 mg/1 g

Drug Facts

Active ingredient

Ethyl Alcohol 63.00%

Purpose

Antiseptic

Keep Out of Reach of Children

If swallowed get medical help or contact a Poison Control Center right away.

Uses

For handwashing to decrease bacteria on the skin.

Warnings

For external use only: Hands. Flammable. Keep away from fire or flame. When using this product: keep out of eyes. In case of contact with eyes, flush thoroughly with water. Avoid contact with broken skin. Do not inhale or ingest. Stop use and ask a doctor: if irritation and redness develop. Condition persists for more than 72 hours.

Directions

Wet hands thoroughly with product and allow to dry without wiping. For children under 6, use only under adult supervision. Not recommended for infants.

Inactive Ingredients

Carbomer, DMDM Hydantoin, Fragrance, Isopropanol, Propylene Glycol, Tocopheryl Acetate, Triethanolamine, Water.